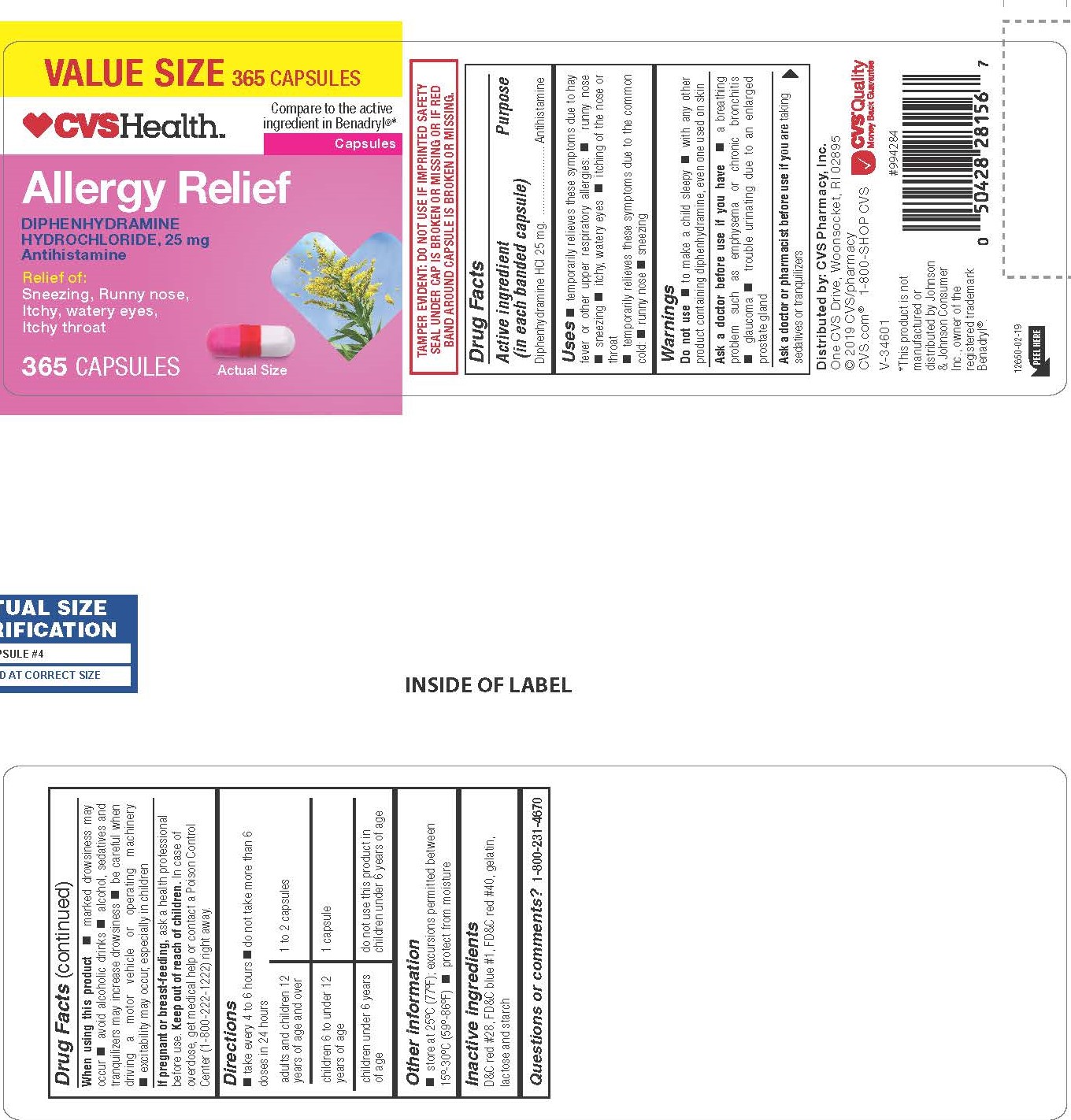 DRUG LABEL: DIPHENHYDRAMINE HYDROCHLORIDE
NDC: 69842-825 | Form: CAPSULE
Manufacturer: CVS Pharmacy, Inc.
Category: otc | Type: HUMAN OTC DRUG LABEL
Date: 20241202

ACTIVE INGREDIENTS: DIPHENHYDRAMINE HYDROCHLORIDE 25 mg/1 1
INACTIVE INGREDIENTS: D&C RED NO. 28; GELATIN; LACTOSE MONOHYDRATE; FD&C BLUE NO. 1; FD&C RED NO. 40; STARCH, CORN

0835 - CVS

Drug Facts

Active ingredient (in each banded capsule)

Diphenhydramine HCI 25 mg.

Purpose

Antihistamine

Uses

- temporarily relieves these symptoms due to hay fever or other upper respiratory allergies: 
- runny nose 
- sneezing 
- itchy, watery eyes 
- itching of the nose or throat
- temporarily relieves these symptoms due to the common cold: 
- runny nose 
- sneezing

Warnings

Do not use

- to make a child sleepy 
- with any other product containing diphenhydramine, even one used on skin

Ask a doctor before use if you have

- a breathing problem such as emphysema or chronic bronchitis 
- glaucoma 
- trouble urinating due to an enlarged prostate gland

Ask a doctor or pharmacist before use if you are

taking sedatives or tranquilizers

When using this product

- marked drowsiness may occur 
- avoid alcoholic drinks
- alcohol, sedatives and tranquilizers may increase drowsiness 
- be careful when driving a motor vehicle or operating machinery 
- excitability may occur, especially in children

If pregnant or breast-feeding,

ask a health professional before use.

OVERDOSAGE

In case of overdose, get medical help or contact a Poison Control Center (1-800-222-1222) right away.

Directions

- take every 4 to 6 hours 
- do not take more than 6 doses in 24 hours

adults and children 12 years of age and over | 1 to 2 capsules
children 6 to under 12 years of age | 1 capsule
children under 6 years of age | do not use this product in children under 6 years of age

Other information

- store at 25ºC (77ºF); excursions permitted between 15º-30ºC (59º-86ºF) 
- protect from moisture 
- see end flap for expiration date and lot number

Inactive ingredients

D&C red #28, FD&C blue #1, FD&C red #40, gelatin, lactose and starch

Questions or comments?

1-800-231-4670

TAMPER EVIDENT: DO NOT USE IF IMPRINTED SAFETY SEAL UNDER CAP IS BROKEN OR MISSING OR IF RED BAND AROUND CAPSULE IS BROKEN OR MISSING.

RETAIN CARTON FOR COMPLETE PRODUCT INFORMATION

*This product is not manufactured or distributed by Johnson & Johnson Consumer Inc., owner of the registered trademark Benadryl®.

Distributed by: CVS Pharmacy, Inc.

One CVS Drive, Woonsocket, RI 02895

© 2018 CVS/pharmacy

CVS.com® 1-800-SHOP CVS

V-34601

PACKAGE LABEL

CVSHealth

Compare to the active ingredient in Benadryl®*

Allergy Relief

DIPHENHYDRAMINE HYDROCHLORIDE,

25 mg - Antihistamine

Relief of:

Sneezing, Runny nose,

Itchy, watery eyes, Itchy throat

365 CAPSULES